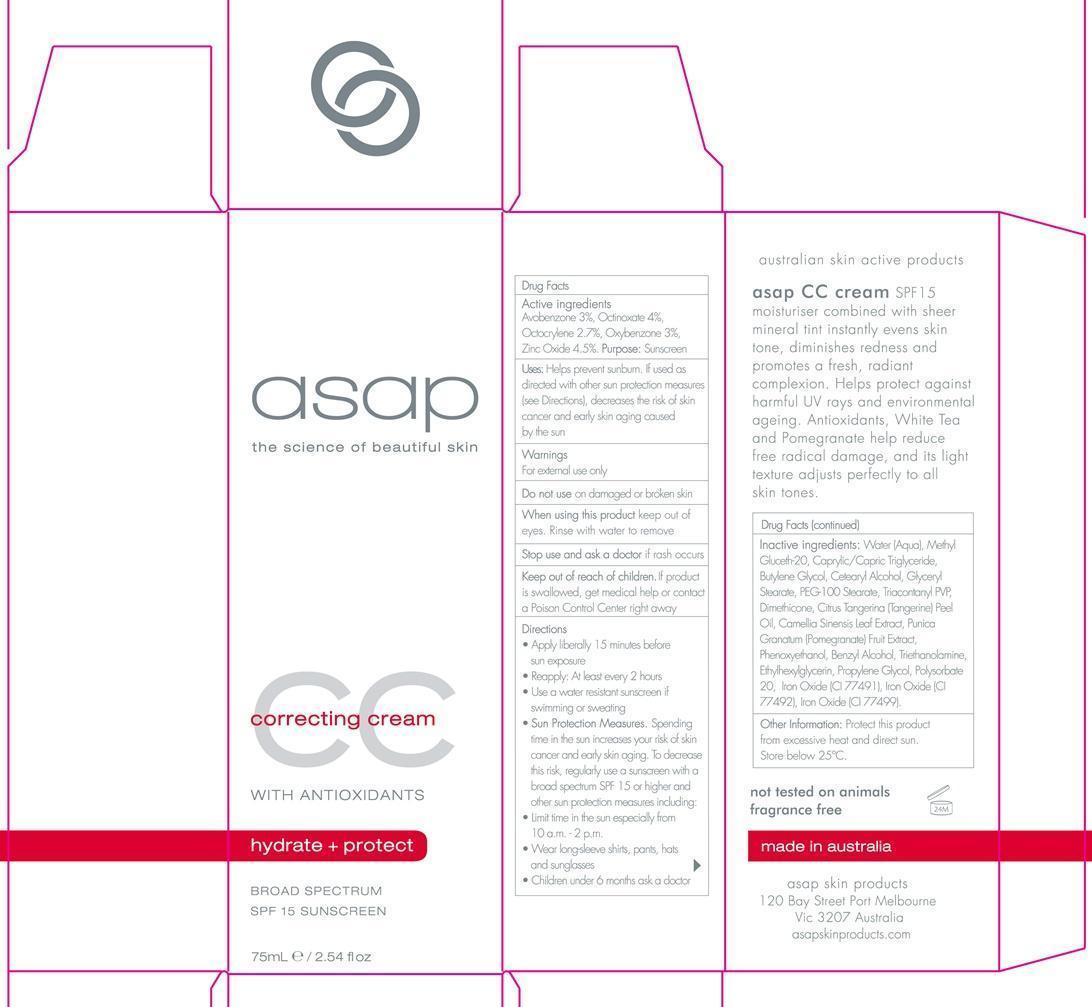 DRUG LABEL: correcting cream Broad Spectrum SPF 15
NDC: 76261-126 | Form: LOTION
Manufacturer: AUSTRALIAN SKIN PRODUCTS PTY LTD
Category: otc | Type: HUMAN OTC DRUG LABEL
Date: 20140804

ACTIVE INGREDIENTS: AVOBENZONE 3 g/100 mL; OCTINOXATE 4 g/100 mL; OCTOCRYLENE 2.7 g/100 mL; OXYBENZONE 3 g/100 mL; ZINC OXIDE 4.5 g/100 mL
INACTIVE INGREDIENTS: WATER; METHYL GLUCETH-20; MEDIUM-CHAIN TRIGLYCERIDES; BUTYLENE GLYCOL; CETOSTEARYL ALCOHOL; GLYCERYL MONOSTEARATE; PEG-100 STEARATE; TRICONTANYL POVIDONE; DIMETHICONE; MANDARIN OIL; GREEN TEA LEAF; POMEGRANATE; PHENOXYETHANOL; BENZYL ALCOHOL; TROLAMINE; ETHYLHEXYLGLYCERIN; PROPYLENE GLYCOL; POLYSORBATE 20; FERRIC OXIDE RED ; FERRIC OXIDE YELLOW; FERROSOFERRIC OXIDE

CC cream Broad Spectrum SPF 15

Active ingredients Purpose

Avobenzone 3% Sunscreen

Octinoxate 4% Sunscreen

Oxybenzone 3% Sunscreen

Zinc Oxide 4.5% Sunscreen

PURPOSE

Uses: Helps prevent sunburn. If used as directed with other sun protection measures (see Directions) decreases the risk of skin cancer and early skin aging caused by the sun.

Keep out of reach of children. If product is swallowed, get medical help or contact a Poison Control Center right away.

Stop use and ask a doctor if rash occurs.

Warnings

For external use only

Do not use on damaged or broken skin

When using this product keep out eye. Rinse with water to remove.

Directions

Apply liberally 15 minutes before sun exposure

Reapply: at least every 2 hours

Use a water resistant sunscreen if swimming or sweating

Sun Protection Measures. Spending time in the sun increases your risk of skin cancer and early skin aging. To decrease this risk , regularly use a sunscreen with a broad spectrum SPF 15 or higher and other sun protection measures including:

Limit time in the sun especially from 10 a.m. - 2 p.m.

Wear long-sleeve Shirts, pants, hats and sunglasses

children under 6 months ask a doctor

INACTIVE INGREDIENT

Inactive ingredients: Water (Aqua), Methyl Gluceth-20, Caprylic/Capric Triglyceride, Butylene Glycol, Cetearyl Alcohol, Glyceryl Stearate, PEG-100 Stearate, Triacontanyl PVP, Dimethicone, Citrus Tangerina (Tangerine) Peel Oil, Camellia Sinensis Leaf Extract, Punica Granatum (Pomegranate) Fruit Extract, Phenoxyethanol, Benzyl Alcohol, Triethanolamine, Ethylhexylglycerin, Propylene Glycol, Polysorbate 20, Iron Oxide (CI 77491), Iron Oxide (CI 77492), Iron Oxide (CI 77499).

PACKAGE LABEL

asap

the science of beautiful skin
correcting cream

with antixidants

hydrate + protect
Broad Spectrum SPF 15 sunscreen
75 mL/ 2.54 fl oz